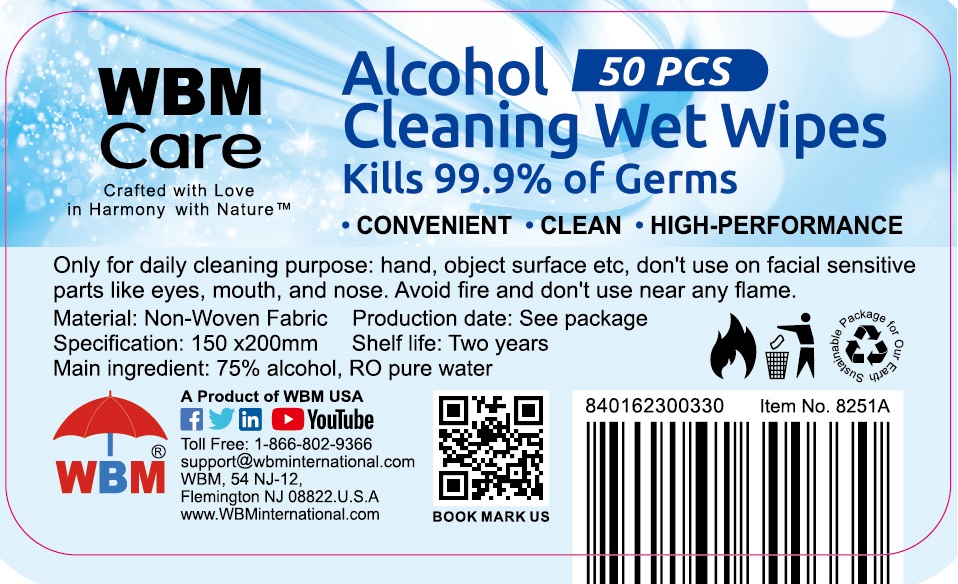 DRUG LABEL: WBM CARE Alcohol cleaning wet wipes
NDC: 78724-004 | Form: SWAB
Manufacturer: Jiebao Daily Chemical (Xiangxi)Co.,Ltd
Category: otc | Type: HUMAN OTC DRUG LABEL
Date: 20200720

ACTIVE INGREDIENTS: ALCOHOL 75 g/100 g
INACTIVE INGREDIENTS: water

alcohol Wipes

Active Ingredient

Alcohol 75%

Purpose

Antiseptic

USE

- Antiseptic
- For handwasing to decrease bacteria on the skin; after assisting ill person; and before contact with a person under medical care treatment
- Apply topically to the skin to help revent cross-contamination.
- Recommended for repeated use.
- Dries in seconds.

Warning

- Flammable, keep away from fire or flame. For external use only.
- When using this product, Do not use in or near the eyes. In case of contact, rinse eyes thoroughly with water.

- Discontinue use, if irritaion and redness develop. If condition persists for more than 72 hours, consult a physician.

KEEP OUT OF REACH OF CHILDREN

●If swallowed, get medical help or contact a Poison Contrl Center right away.

Directions

- Wipe hands, fingers, interdigirtal areas and wrists throughly with towelette. Be sure to utilze the entire wipe surface. Allow to dry.
- If hands are visibly soilde or contaminated, use first wie to clean hands, then discard wipe. Sanitize with a second wipe.
- Discard after single use.

Inactive ingredients

water